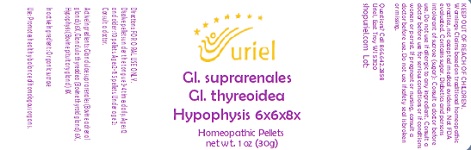 DRUG LABEL: GI. suprarenales GI. thyreoidea Hypophysis 6x6x8x
NDC: 48951-5131 | Form: PELLET
Manufacturer: Uriel Pharmacy Inc.
Category: homeopathic | Type: HUMAN OTC DRUG LABEL
Date: 20230915

ACTIVE INGREDIENTS: BOS TAURUS ADRENAL GLAND 6 [hp_X]/1 1; BOS TAURUS PITUITARY GLAND 8 [hp_X]/1 1; THYROID, UNSPECIFIED 6 [hp_X]/1 1
INACTIVE INGREDIENTS: SUCROSE

GI. suprarenales GI. thyreoidea Hypophysis 6x6x8x

INDICATIONS AND USAGE

Directions: FOR ORAL USE ONLY.

DOSAGE AND ADMINISTRATION

Dissolve pellets under the tongue 3-4 times daily. Ages 12 and older: 10 pellets. Ages 2-11: 5 pellets. Under age 2: Consult a doctor.

ACTIVE INGREDIENT

Active Ingredients: Glandulae suprarenales (Bovine adrenal glands) 6X, Glandula thyreoidea (Bovine thyroid gland) 6X, Hypophysis (Bovine pituitary gland) 8X

Inactive Ingredient: Organic sucrose

PURPOSE

Use: Promotes healthy balance of homologous organs.

KEEP OUT OF REACH OF CHILDREN.

WARNINGS

Warnings: Claims based on traditional homeopathic practice, not accepted medical evidence. Not FDA evaluated. Contains sugar. Diabetics and persons intolerant of sucrose (sugar): Consult a doctor before use. Do not use if allergic to any ingredient. Consult a doctor before use for serious conditions or if conditions worsen or persist. If pregnant or nursing, consult a doctor before use. Do not use if safety seal is broken or missing.

Questions? Call 866.642.2858
Uriel, East Troy WI 53120
shopuriel.com Lot: